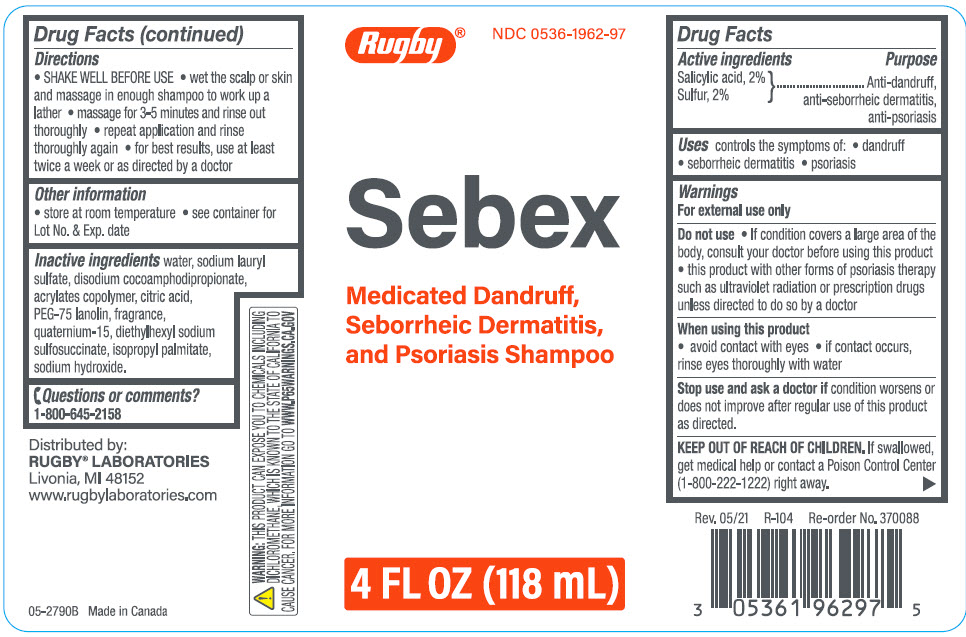 DRUG LABEL: Sebex
NDC: 0536-1962 | Form: SHAMPOO
Manufacturer: Rugby Laboratories
Category: otc | Type: HUMAN OTC DRUG LABEL
Date: 20240301

ACTIVE INGREDIENTS: salicylic acid 20 mg/1000 mL; sulfur 20 mg/1000 mL
INACTIVE INGREDIENTS: Water; Sodium Lauryl Sulfate; Disodium Cocoamphodipropionate; Citric Acid Monohydrate; PEG-75 Lanolin; Quaternium-15; Docusate Sodium; Isopropyl Palmitate; Sodium Hydroxide

Rugby Sebex Medicated Dandruff, Seborrheic Dermatitis, and Psoriasis Shampoo

Drug Facts

ACTIVE INGREDIENT

Active ingredients | Purpose
Salicylic Acid, 2% } Sulfur, 2% | Anti-dandruff, anti-seborrheic dermatitis, anti-psoriasis

Uses

controls the symptoms of:

- dandruff
- seborrheic dermatitis
- psoriasis

Warnings

For external use only

Do not use

- If condition covers a large area of the body, consult your doctor before using this product
- this product with other forms of psoriasis therapy such as ultraviolet radiation or prescription drugs unless directed to do so by a doctor

When using this product

- avoid contact with eyes
- If contact occurs, rinse eyes thoroughly with water

Stop use and ask a doctor if condition worsens or does not improve after regular use of this product as directed.

KEEP OUT OF REACH OF CHILDREN. If swallowed, get medical help or contact a Poison Control Center (1-800-222-1222) right away.

Directions

- SHAKE WELL BEFORE USE
- wet the scalp or skin and massage in enough shampoo to work up a lather
- massage for 3-5 minutes and rinse out thoroughly
- repeat application and rinse thoroughly again
- for best results, use at least twice a week or as directed by a doctor

Other information

- store at room temperature
- see container for Lot No. & Exp. date

Inactive ingredients

water, sodium lauryl sulfate, disodium cocoamphodipropionate, acrylates copolymer, citric acid, PEG-75 lanolin, fragrance, quaternium-15, diethylhexyl sodium sulfosuccinate, isopropyl palmitate, sodium hydroxide.

Questions or comments?

1-800-645-2158

Distributed by:
RUGBY® LABORATORIES
Livonia, MI 48152

PRINCIPAL DISPLAY PANEL - 118 mL Bottle Label

Rugby®

NDC 0536-1962-97

Sebex

Medicated Dandruff,
Seborrheic Dermatitis,
and Psoriasis Shampoo

4 FL OZ (118 mL)